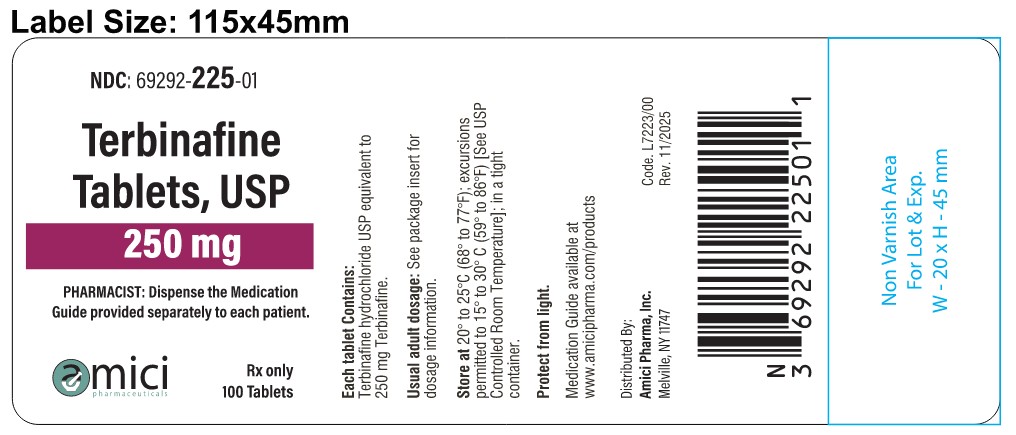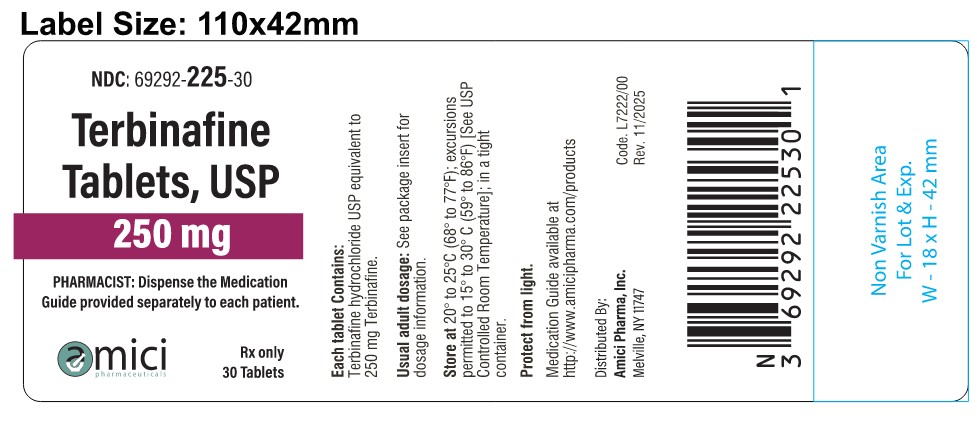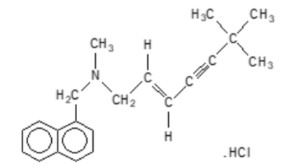 DRUG LABEL: TERBINAFINE HYDROCHLORIDE
NDC: 69292-225 | Form: TABLET
Manufacturer: Amici Pharma, Inc.
Category: prescription | Type: HUMAN PRESCRIPTION DRUG LABEL
Date: 20260218

ACTIVE INGREDIENTS: TERBINAFINE HYDROCHLORIDE 250 mg/1 1
INACTIVE INGREDIENTS: SILICON DIOXIDE; CROSCARMELLOSE SODIUM; HYPROMELLOSE, UNSPECIFIED; MAGNESIUM STEARATE; MICROCRYSTALLINE CELLULOSE

HIGHLIGHTS OF PRESCRIBING INFORMATION

These highlights do not include all the information needed to use TERBINAFINE TABLETS safely and effectively.
See full prescribing information for TERBINAFINE TABLETS.
TERBINAFINE tablets, for oral use Initial U.S. Approval: 1992

1 INDICATIONS AND USAGE

Terbinafine tablets are an allylamine antifungal indicated for the treatment of onychomycosis of the toenail or fingernail due to dermatophytes (tinea unguium) (1)

2 DOSAGE AND ADMINISTRATION

- Prior to administering, evaluate patients for evidence of chronic or active liver disease. (2.1)
- Fingernail onychomycosis: One tablet, once daily for 6 weeks (2.2)
- Toenail onychomycosis: One tablet, once daily for 12 weeks (2.2)

3 DOSAGE FORMS AND STRENGTHS

Tablet, 250 mg (3)

4 CONTRAINDICATIONS

- Chronic or active liver disease. (4)
- History of allergic reaction to oral terbinafine because of the risk of anaphylaxis. (4)

5 WARNINGS AND PRECAUTIONS

- Liver failure, sometimes leading to liver transplant or death, has occurred with the use of oral terbinafine. Obtain pretreatment serum transaminases. Prior to initiating treatment and periodically during therapy, assess liver function tests. Discontinue terbinafine tablets if liver injury develops. (5.1)
- Taste disturbance, including taste loss, has been reported with the use of terbinafine tablets. Taste disturbance can be severe, may be prolonged, or may be permanent. Discontinue terbinafine tablets if taste disturbance occurs. (5.2)
- Smell disturbance, including loss of smell, has been reported with the use of terbinafine tablets. Smell disturbance may be prolonged, or may be permanent. Discontinue terbinafine tablets if smell disturbance occurs. (5.3)
- Depressive symptoms have been reported with terbinafine use. Prescribers should be alert to the development of depressive symptoms. (5.4)
- Severe neutropenia has been reported. If the neutrophil count is less than or equal to 1000 cells/mm^3, terbinafine tablets should be discontinued. (5.5)
- Stevens-Johnson syndrome, toxic epidermal necrolysis, erythema multiforme, exfoliative dermatitis, bullous dermatitis, and drug reaction with eosinophilia and systemic symptoms (DRESS) syndrome have been reported with oral terbinafine use. If signs or symptoms of drug reaction occur, treatment with terbinafine tablets should be discontinued. (5.6)

6 ADVERSE REACTIONS

Common (greater than 2% of patients treated with terbinafine tablets) reported adverse events include headache, diarrhea, rash, dyspepsia, liver enzyme abnormalities, pruritus, taste disturbance, nausea, abdominal pain, and flatulence. (6.1)

To report SUSPECTED ADVERSE REACTIONS, contact Amici Pharma, Inc. at 1-866-760-2646 or FDA at 1-800-FDA-1088 or www.fda.gov/medwatch.

7 DRUG INTERACTIONS

Terbinafine is an inhibitor of CYP450 2D6 isozyme and has an effect on metabolism of desipramine. Drug interactions have also been noted with cimetidine, fluconazole, cyclosporine, rifampin, and caffeine. (7.1)

FULL PRESCRIBING INFORMATION

1 INDICATIONS AND USAGE

Terbinafine tablets are indicated for the treatment of onychomycosis of the toenail or fingernail due to dermatophytes (tinea unguium).

Prior to initiating treatment, appropriate nail specimens for laboratory testing [potassium hydroxide (KOH) preparation, fungal culture, or nail biopsy] should be obtained to confirm the diagnosis of onychomycosis.

2 DOSAGE AND ADMINISTRATION

2.1 Assessment Prior to Initiation

Before administering terbinafine tablets, evaluate patients for evidence of chronic or active liver disease [see Contraindications (4) and Warnings and Precautions (5.1)].

2.2 Dosage

Fingernail onychomycosis: One 250 mg tablet once daily for 6 weeks.

Toenail onychomycosis: One 250 mg tablet once daily for 12 weeks.

The optimal clinical effect is seen some months after mycological cure and cessation of treatment. This is related to the period required for outgrowth of healthy nail.

3 DOSAGE FORMS AND STRENGTHS

Tablet, 250 mg White Round, Flat, beveled edge tablets debossed with "128" on one side and "A" on the other side.

4 CONTRAINDICATIONS

Terbinafine tablets are contraindicated in patients with:

- Chronic or active liver disease [see Warnings and Precautions (5.1)]
- History of allergic reaction to oral terbinafine because of the risk of anaphylaxis [see Adverse Reactions (6.2)] .

5 WARNINGS AND PRECAUTIONS

5.1 Hepatotoxicity

Terbinafine tablets are contraindicated for patients with chronic or active liver disease. Before prescribing terbinafine tablets, perform liver function tests because hepatotoxicity may occur in patients with and without preexisting liver disease. Cases of liver failure, some leading to liver transplant or death, have occurred with the use of terbinafine tablets in individuals with and without preexisting liver disease.

In the majority of liver cases reported in association with use of terbinafine tablets, the patients had serious underlying systemic conditions. The severity of hepatic events and/or their outcome may be worse in patients with active or chronic liver disease. Periodic monitoring of liver function tests is recommended. Discontinue terbinafine tablets if biochemical or clinical evidence of liver injury develops.

Warn patients prescribed terbinafine tablets and/or their caregivers to report immediately to their healthcare providers any symptoms or signs of persistent nausea, anorexia, fatigue, vomiting, right upper abdominal pain or jaundice, dark urine, or pale stools. Advise patients with these symptoms to discontinue taking oral terbinafine, and immediately evaluate the patient's liver function.

5.2 Taste Disturbance Including Loss of Taste

Taste disturbance, including taste loss, has been reported with the use of terbinafine tablets. It can be severe enough to result in decreased food intake, weight loss, anxiety, and depressive symptoms. Taste disturbance may resolve within several weeks after discontinuation of treatment, but may be prolonged (greater than 1 year), or may be permanent. If symptoms of a taste disturbance occur, terbinafine tablets should be discontinued.

5.3 Smell Disturbance Including Loss of Smell

Smell disturbance, including loss of smell, has been reported with the use of terbinafine tablets. Smell disturbance may resolve after discontinuation of treatment, but may be prolonged (greater than 1 year), or may be permanent. If symptoms of a smell disturbance occur, terbinafine tablets should be discontinued.

5.4 Depressive Symptoms

Depressive symptoms have occurred during postmarketing use of terbinafine tablets. Prescribers should be alert to the development of depressive symptoms, and patients should be instructed to report depressive symptoms to their physician.

5.5 Hematologic Effects

Transient decreases in absolute lymphocyte counts (ALCs) have been observed in controlled clinical trials. In placebo-controlled trials, 8/465 subjects receiving terbinafine tablets (1.7%) and 3/137 subjects receiving placebo (2.2%) had decreases in ALC to below 1000/mm^3 on 2 or more occasions. In patients with known or suspected immunodeficiency, physicians should consider monitoring complete blood counts if treatment continues for more than 6 weeks. Cases of severe neutropenia have been reported. These were reversible upon discontinuation of terbinafine tablets, with or without supportive therapy. If clinical signs and symptoms suggestive of secondary infection occur, a complete blood count should be obtained. If the neutrophil count is less than or equal to 1000 cells/ mm^3, terbinafine tablets should be discontinued and supportive management started.

5.6 Serious Skin/Hypersensitivity Reactions

There have been postmarketing reports of serious skin/hypersensitivity reactions [e.g., Stevens-Johnson syndrome, toxic epidermal necrolysis, erythema multiforme, exfoliative dermatitis, bullous dermatitis, and drug reaction with eosinophilia and systemic symptoms (DRESS) syndrome]. Manifestations of DRESS syndrome may include cutaneous reaction (such as rash or exfoliative dermatitis), eosinophilia, and one or more organ complications such as hepatitis, pneumonitis, nephritis, myocarditis, and pericarditis. If progressive skin rash or signs/symptoms of the above drug reactions occur, treatment with terbinafine tablets should be discontinued.

5.7 Lupus Erythematosus

During postmarketing experience, precipitation and exacerbation of cutaneous and systemic lupus erythematosus have been reported in patients taking terbinafine tablets. Terbinafine tablets should be discontinued in patients with clinical signs and symptoms suggestive of lupus erythematosus.

5.8 Thrombotic Microangiopathy

Cases of thrombotic microangiopathy (TMA), including thrombotic thrombocytopenic purpura and hemolytic uremic syndrome, some fatal, have been reported with terbinafine. Discontinue terbinafine if clinical symptoms and laboratory findings consistent with TMA occur. The findings of unexplained thrombocytopenia and anemia should prompt further evaluation and consideration of diagnosis of TMA.

6 ADVERSE REACTIONS

6.1 Clinical Trials Experience

Because clinical trials are conducted under widely varying conditions, adverse reaction rates in the clinical trials of a drug cannot be directly compared to rates in the clinical trials of another drug and may not reflect the rates observed in practice.

The most frequently reported adverse events observed in the 3 U.S./Canadian placebo-controlled trials are listed in the Table 1. The adverse events reported encompass gastrointestinal symptoms (including diarrhea, dyspepsia, and abdominal pain), liver test abnormalities, rashes, urticaria, pruritus, and taste disturbances. Changes in the ocular lens and retina have been reported following the use of terbinafine in controlled trials. The clinical significance of these changes is unknown. In general, the adverse events were mild, transient, and did not lead to discontinuation from study participation.

Table 1. Most frequently reported adverse events observed in the 3 U.S./Canadian placebo-controlled trials

 | Adverse Event |  | Discontinuation
 | Terbinafine Tablets (%) n = 465 | Placebo (%) n = 137 | Terbinafine Tablets (%) n = 465 | Placebo (%) n = 137
Headache | 12.9 | 9.5 | 0.2 | 0
Gastrointestinal Symptoms:
Diarrhea | 5.6 | 2.9 | 0.6 | 0
Dyspepsia | 4.3 | 2.9 | 0.4 | 0
Abdominal Pain | 2.4 | 1.5 | 0.4 | 0
Nausea | 2.6 | 2.9 | 0.2 | 0
Flatulence | 2.2 | 2.2 | 0 | 0
Dermatological Symptoms:
Rash | 5.6 | 2.2 | 0.9 | 0.7
Pruritus | 2.8 | 1.5 | 0.2 | 0
Urticaria | 1.1 | 0 | 0 | 0
Liver Enzyme Abnormalities* | 3.3 | 1.4 | 0.2 | 0
Taste Disturbance | 2.8 | 0.7 | 0.2 | 0
Visual Disturbance | 1.1 | 1.5 | 0.9 | 0
* Liver enzyme abnormalities greater than or equal to 2 times the upper limit of normal range.

6.2 Postmarketing Experience

The following adverse events have been identified during post-approval use of terbinafine tablets. Because these events are reported voluntarily from a population of uncertain size, it is not always possible to reliably estimate their frequency or establish a causal relationship to drug exposure.

Blood and lymphatic system disorders: Pancytopenia, agranulocytosis, severe neutropenia, thrombocytopenia, anemia, thrombotic microangiopathy (TMA), including thrombotic thrombocytopenic purpura and hemolytic uremic syndrome [see Warnings and Precautions (5.5, 5.8)]

Immune system disorders: Serious hypersensitivity reactions e.g., angioedema and allergic reactions (including anaphylaxis), precipitation and exacerbation of cutaneous and systemic lupus erythematosus [see Warnings and Precautions (5.7)], serum sickness-like reaction

Psychiatric disorders: Anxiety and depressive symptoms independent of taste disturbance have been reported with use of terbinafine tablets. In some cases, depressive symptoms have been reported to subside with discontinuance of therapy and to recur with reinstitution of therapy [see Warnings and Precautions (5.4)].

Nervous system disorders: Cases of taste disturbance, including taste loss, have been reported with the use of terbinafine tablets. It can be severe enough to result in decreased food intake, weight loss, anxiety, and depressive symptoms. Cases of smell disturbance, including smell loss, have been reported with the use of terbinafine tablets [see Warnings and Precautions (5.2, 5.3)]. Cases of paresthesia and hypoesthesia have been reported with the use of terbinafine tablets.

Eye disorders: Visual field defects, reduced visual acuity

Ear and labyrinth disorders: Hearing impairment, vertigo, tinnitus

Vascular disorders: Vasculitis

Gastrointestinal disorders: Pancreatitis, vomiting

Hepatobiliary disorders: Cases of liver failure some leading to liver transplant or death [see Warnings and Precautions (5.1)], idiosyncratic and symptomatic hepatic injury. Cases of hepatitis, cholestasis, and increased hepatic enzymes [see Warnings and Precautions (5.1)] have been seen with the use of terbinafine tablets.

Skin and subcutaneous tissue disorders: Serious skin reactions [e.g., Stevens-Johnson syndrome, toxic epidermal necrolysis, erythema multiforme, exfoliative dermatitis, bullous dermatitis, and drug reaction with eosinophilia and systemic symptoms (DRESS) syndrome] [see Warnings and Precautions (5.6)], acute generalized exanthematous pustulosis, psoriasiform eruptions or exacerbation of psoriasis, photosensitivity reactions, hair loss

Musculoskeletal and connective tissue disorders: Rhabdomyolysis, arthralgia, myalgia

General disorders and administration site conditions: Malaise, fatigue, influenza-like illness, pyrexia

Investigations: Altered prothrombin time (prolongation and reduction) in patients concomitantly treated with warfarin and increased blood creatine phosphokinase have been reported.

* Liver enzyme abnormalities greater than or equal to 2 times the upper limit of normal range.

7 DRUG INTERACTIONS

7.1 Drug-Drug Interactions

In vivo studies have shown that terbinafine is an inhibitor of the CYP450 2D6 isozyme. Drugs predominantly metabolized by the CYP450 2D6 isozyme include the following drug classes: tricyclic antidepressants, selective serotonin reuptake inhibitors, beta-blockers, antiarrhythmics class 1C (e.g., flecainide and propafenone) and monoamine oxidase inhibitors Type B. Coadministration of terbinafine tablets should be done with careful monitoring and may require a reduction in dose of the 2D6-metabolized drug. In a study to assess the effects of terbinafine on desipramine in healthy volunteers characterized as normal metabolizers, the administration of terbinafine resulted in a 2-fold increase in Cmax and a 5-fold increase in area under the curve (AUC). In this study, these effects were shown to persist at the last observation at 4 weeks after discontinuation of terbinafine tablets. In studies in healthy subjects characterized as extensive metabolizers of dextromethorphan (antitussive drug and CYP2D6 probe substrate), terbinafine increases the dextromethorphan/dextrorphan metabolite ratio in urine by 16- to 97-fold on average. Thus, terbinafine may convert extensive CYP2D6 metabolizers to poor metabolizer status.

In vitro studies with human liver microsomes showed that terbinafine does not inhibit the metabolism of tolbutamide, ethinylestradiol, ethoxycoumarin, cyclosporine, cisapride and fluvastatin. In vivo drug-drug interaction studies conducted in healthy volunteer subjects showed that terbinafine does not affect the clearance of antipyrine or digoxin. Terbinafine decreases the clearance of caffeine by 19%. Terbinafine increases the clearance of cyclosporine by 15%.

The influence of terbinafine on the pharmacokinetics of fluconazole, cotrimoxazole (trimethoprim and sulfamethoxazole), zidovudine or theophylline was not considered to be clinically significant.

Coadministration of a single dose of fluconazole (100 mg) with a single dose of terbinafine resulted in a 52% and 69% increase in terbinafine Cmax and AUC, respectively. Fluconazole is an inhibitor of CYP2C9 and CYP3A enzymes. Based on this finding, it is likely that other inhibitors of both CYP2C9 and CYP3A4 (e.g., ketoconazole, amiodarone) may also lead to a substantial increase in the systemic exposure (Cmax and AUC) of terbinafine when concomitantly administered.

There have been spontaneous reports of increase or decrease in prothrombin times in patients concomitantly taking oral terbinafine and warfarin, however, a causal relationship between terbinafine tablets and these changes has not been established.

Terbinafine clearance is increased 100% by rifampin, a CYP450 enzyme inducer, and decreased 33% by cimetidine, a CYP450 enzyme inhibitor. Terbinafine clearance is unaffected by cyclosporine. There is no information available from adequate drug-drug interaction studies with the following classes of drugs: oral contraceptives, hormone replacement therapies, hypoglycemics, phenytoins, thiazide diuretics, and calcium channel blockers.

7.2 Food Interactions

An evaluation of the effect of food on terbinafine tablets was conducted. An increase of less than 20% of the AUC of terbinafine was observed when terbinafine tablets were administered with food. Terbinafine tablets can be taken with or without food.

8 USE IN SPECIFIC POPULATIONS

8.1 Pregnancy

Risk Summary

Available data from postmarketing cases on the use of terbinafine tablets in pregnant women are insufficient to evaluate a drug-associated risk of major birth defects, miscarriage, or adverse maternal or fetal outcomes.

In animal reproduction studies, terbinafine did not cause malformations or any harm to the fetus when administered to pregnant rabbits and rats during the period of organogenesis at oral doses up to 12 and 23 times the maximum recommended human dose (MRHD) of 250 mg/day, respectively (see data).

All pregnancies have a background risk of birth defect, loss, or other adverse outcomes. The background risk of major birth defects and miscarriage for the indicated population is unknown; however, in the U.S. general population, the estimated background risk of major birth defects is 2% to 4% and of miscarriage is 15% to 20% of clinically recognized pregnancies.

Data

Animal Data

In embryo-fetal development studies in rats and rabbits, pregnant animals received orally (by gavage) doses of terbinafine up to 300 mg/kg/day, during the period of organogenesis. There were no maternal or embryo-fetal effects in either species up to the maximum dose tested. The 300 mg/kg/day dose level in rats and rabbits corresponds to 23 and 12 times the MRHD [based on body surface area (BSA) comparisons], respectively.

In a rat peri-and postnatal development study, terbinafine doses of up to 300 mg/kg/day (12 times the MRHD based on BSA comparisons) given by oral gavage during late pregnancy and lactation (Day 15 of gestation to day 20 post-partum) had no adverse effects on parturition and lactation.

8.2 Lactation

Risk Summary

After oral administration, terbinafine is present in human milk. However, there are no data on the effects on the breastfed child or on milk production. The developmental and health benefits of breastfeeding should be considered along with the mother's clinical need for terbinafine tablets and any potential adverse effects on the breastfed child from terbinafine tablets or from the underlying maternal condition.

8.4 Pediatric Use

The safety and efficacy of terbinafine tablets have not been established in pediatric patients with onychomycosis.

8.5 Geriatric Use

Clinical studies of terbinafine tablets did not include sufficient numbers of subjects aged 65 years and over to determine whether they respond differently from younger subjects. Other reported clinical experience has not identified differences in responses between the elderly and younger patients. In general, dose selection for an elderly patient should be cautious, usually starting at the low end of the dosing range, reflecting the greater frequency of decreased hepatic, renal, or cardiac function, and of concomitant disease or other drug therapy.

8.6 Renal Impairment

In patients with renal impairment (creatinine clearance less than or equal to 50 mL/min), the use of terbinafine tablets has not been adequately studied.

8.7 Hepatic Impairment

Terbinafine tablets are contraindicated for patients with chronic or active liver disease [see Contraindications (4) and Warnings and Precautions (5.1)]. Cases of liver failure, some leading to liver transplant or death, have occurred with the use of terbinafine tablets in individuals with and without preexisting liver disease. The severity of hepatic events and/or their outcome may be worse in patients with active or chronic liver disease.

10 OVERDOSAGE

Clinical experience regarding overdose with oral terbinafine is limited. Doses up to 5 grams (20 times the therapeutic daily dose) have been taken without inducing serious adverse reactions. The symptoms of overdose included nausea, vomiting, abdominal pain, dizziness, rash, frequent urination, and headache.

11 DESCRIPTION

Terbinafine tablets, USP contain the synthetic allylamine antifungal compound terbinafine hydrochloride USP.

Chemically, terbinafine hydrochloride is (E)-N-(6,6-dimethyl-2-hepten-4-ynyl)-N-methyl-1-naphthalenemethanamine hydrochloride. The molecular formula C21H26CIN with a molecular weight of 327.90, and the following structural formula:

Terbinafine hydrochloride USP is a white to off-white fine crystalline powder. It is freely soluble in methanol and methylene chloride, soluble in ethanol, and slightly soluble in water.

Each tablet contains:

Active Ingredient: Terbinafine hydrochloride USP (equivalent to 250 mg of terbinafine)

Inactive Ingredients: Colloidal silicon dioxide, caroscarmellose sodium, hypromellose, magnesium stearate, microcrystalline cellulose.

12 CLINICAL PHARMACOLOGY

12.1 Mechanism of Action

Terbinafine is an allylamine antifungal [see Clinical Pharmacology (12.4)].

12.2 Pharmacodynamics

The pharmacodynamics of terbinafine tablets is unknown.

12.3 Pharmacokinetics

Following oral administration, terbinafine is well absorbed (greater than 70%) and the bioavailability of terbinafine tablets as a result of first-pass metabolism is approximately 40%. Peak plasma concentrations of 1 mcg/mL appear within 2 hours after a single 250 mg dose; the AUC is approximately 4.56 mcg.h/mL. An increase in the AUC of terbinafine of less than 20% is observed when terbinafine tablets are administered with food.

In plasma, terbinafine is greater than 99% bound to plasma proteins and there are no specific binding sites. At steady-state, in comparison to a single dose, the peak concentration of terbinafine is 25% higher and plasma AUC increases by a factor of 2.5; the increase in plasma AUC is consistent with an effective half-life of ~36 hours. Terbinafine is distributed to the sebum and skin. A terminal half-life of 200 to 400 hours may represent the slow elimination of terbinafine from tissues such as skin and adipose. Prior to excretion, terbinafine is extensively metabolized by at least 7 CYP isoenzymes with major contributions from CYP2C9, CYP1A2, CYP3A4, CYP2C8, and CYP2C19. No metabolites have been identified that have antifungal activity similar to terbinafine. Approximately 70% of the administered dose is eliminated in the urine.

In patients with renal impairment (creatinine clearance less than or equal to 50 mL/min) or hepatic cirrhosis, the clearance of terbinafine is decreased by approximately 50% compared to normal volunteers. No effect of gender on the blood levels of terbinafine was detected in clinical trials. No clinically relevant age-dependent changes in steady-state plasma concentrations of terbinafine have been reported.

12.4 Microbiology

Terbinafine, an allylamine antifungal, inhibits biosynthesis of ergosterol, an essential component of fungal cell membrane, via inhibition of squalene epoxidase enzyme. This results in fungal cell death primarily due to the increased membrane permeability mediated by the accumulation of high concentrations of squalene but not due to ergosterol deficiency. Depending on the concentration of the drug and the fungal species test in vitro, terbinafine hydrochloride may be fungicidal. However, the clinical significance of in vitro data is unknown.

Terbinafine has been shown to be active against most strains of the following microorganisms both in vitro and in clinical infections:

Trichophyton mentagrophytes

Trichophyton rubrum

The following in vitro data are available, but their clinical significance is unknown. In vitro, terbinafine exhibits satisfactory MIC's against most strains of the following microorganisms; however, the safety and efficacy of terbinafine in treating clinical infections due to these microorganisms have not been established in adequate and well-controlled clinical trials:

Candida albicans

Epidermophyton floccosum

Scopulariopsis brevicaulis

Susceptibility Testing

For specific information regarding susceptibility test interpretive criteria and associated test methods and quality control standards recognized by FDA for this drug, please see: https://www.fda.gov/STIC.

13 NONCLINICAL TOXICOLOGY

13.1 Carcinogenesis, Mutagenesis, Impairment of Fertility

In a 28-month oral carcinogenicity study in rats, an increase in the incidence of liver tumors was observed in males at the highest dose tested, 69 mg/kg/day (2 times the MRHD based on AUC comparisons of the parent terbinafine); however, even though dose-limiting toxicity was not achieved at the highest tested dose, higher doses were not tested.

The results of a variety of in vitro (mutations in E. coli and S. typhimurium, DNA repair in rat hepatocytes, mutagenicity in Chinese hamster fibroblasts, chromosome aberration, and sister chromatid exchanges in Chinese hamster lung cells), and in vivo (chromosome aberration in Chinese hamsters, micronucleus test in mice) genotoxicity tests gave no evidence of a mutagenic or clastogenic potential.

Oral reproduction studies in rats at doses up to 300 mg/kg/day (12 times the MRHD based on BSA comparisons) did not reveal any specific effects on fertility or other reproductive parameters. Intravaginal application of terbinafine hydrochloride at 150 mg/day in pregnant rabbits did not increase the incidence of abortions or premature deliveries nor affect fetal parameters.

13.2 Animal Toxicology and/or Pharmacology

A wide range of in vivo studies in mice, rats, dogs, and monkeys, and in vitro studies using rat, monkey, and human hepatocytes suggest that peroxisome proliferation in the liver is a rat-specific finding. However, other effects, including increased liver weights and APTT, occurred in dogs and monkeys at doses giving Css trough levels of the parent terbinafine 2 to 3 times those seen in humans at the MRHD. In a 52-week oral toxicology study conducted in juvenile maturing dogs, increased heart and liver weights were noted in males and signs of CNS disturbance including 3 cases of single episodes of seizures were noted in females at the highest dose tested, 100 mg/kg/day [19 times (males) and 10 times (females) the MRHD based on AUC comparisons of the parent terbinafine]. No treatment related findings were noted at 30 mg/kg/day [1.6 times (males) and 1.9 times (females) the MRHD based on AUC comparisons of the parent terbinafine] in this study.

14 CLINICAL STUDIES

The efficacy of terbinafine tablets in the treatment of onychomycosis is illustrated by the response of subjects with toenail and/or fingernail infections who participated in 3 U.S./Canadian placebo-controlled clinical trials.

Results of the first toenail trial, as assessed at week 48 (12 weeks of treatment with 36 weeks follow-up after completion of therapy), demonstrated mycological cure, defined as simultaneous occurrence of negative KOH plus negative culture, in 70% of subjects. Fifty-nine percent (59%) of subjects experienced effective treatment (mycological cure plus 0% nail involvement or greater than 5mm of new unaffected nail growth); 38% of subjects demonstrated mycological cure plus clinical cure (0% nail involvement).

In a second toenail trial of dermatophytic onychomycosis, in which non dermatophytes were also cultured, similar efficacy against the dermatophytes was demonstrated. The pathogenic role of the nondermatophytes cultured in the presence of dermatophytic onychomycosis has not been established. The clinical significance of this association is unknown.

Results of the fingernail trial, as assessed at week 24 (6 weeks of treatment with 18 weeks follow-up after completion of therapy), demonstrated mycological cure in 79% of subjects, effective treatment in 75% of the subjects, and mycological cure plus clinical cure in 59% of the subjects.

The mean time to overall success was approximately 10 months for the first toenail trial and 4 months for the fingernail trial. In the first toenail trial, for subjects evaluated at least 6 months after achieving clinical cure and at least 1 year after completing therapy with terbinafine tablets, the clinical relapse rate was approximately 15%.

16 HOW SUPPLIED/STORAGE AND HANDLING

Terbinafine Tablets, USP 250 mg are supplied as White Round, Flat, beveled edge tablets debossed with "128" on one side and "A" on other side.

Bottles of 30 NDC 69292-225-30

Bottles of 100 NDC 69292-225-01

Store at 20°C to 25°C (68°F to 77°F); excursions permitted to 15°C to 30°C (59°F to 86°F) [see USP Controlled Room Temperature]. Protect from light.

17 PATIENT COUNSELING INFORMATION

Advise the patient to read the FDA-Approved Medication Guide.

Patients taking terbinafine tablets should receive the following information and instructions:

Advise patients to immediately report to their physician or get emergency help if they experience any of the following symptoms: hives, mouth sores, blistering and peeling of skin, swelling of face, lips, tongue, or throat, difficulty swallowing or breathing. Terbinafine tablets treatment should be discontinued.

Advise patients to immediately report to their physician any symptoms of persistent nausea, anorexia, fatigue, vomiting, right upper abdominal pain, jaundice, dark urine, or pale stools. Terbinafine tablets treatment should be discontinued.
Advise patients to report to their physician any signs of taste disturbance, smell disturbance and/or depressive symptoms, fever, skin eruption, lymph node enlargement, erythema, scaling, loss of pigment, and unusual photosensitivity that can result in a rash. Terbinafine tablets treatment should be discontinued.

Advise patients to minimize exposure to natural and artificial sunlight (tanning beds or UVA/B treatment) while using terbinafine tablets.
Advise patients that if they forget to take terbinafine tablets, to take their tablets as soon as they remember, unless it is less than 4 hours before the next dose is due.

Advise patients to call their physician if they take too many terbinafine tablets.

Advise patients to call their physician if they become pregnant during treatment with terbinafine tablets.

Dispense with Medication Guide available at: www.amicipharma.com/products

Distributed by:

Amici Pharma, Inc.

Melville, NY 11747

Code: L7224/00

Revised: 11/2025

MEDICATION GUIDE

Terbinafine Tablets, USP [Terbinafine (ter BIN na feen)]

What is the most important information I should know about terbinafine tablets?

Terbinafine tablets may cause serious side effects, including:

- Liver problems that can lead to the need for a liver transplant or death .

This can happen in people who have liver problems and in people who have never had liver problems. Tell your doctor right away if you get any of these symptoms of liver problems:

- nausea
- poor appetite
- tiredness
- vomiting
- upper right stomach-area (abdomen) pain
- yellowing of your skin or eyes (jaundice)
- dark (tea-colored) urine
- pale or light colored stools

Your doctor should do a blood test to check you for liver problems before you start treatment with terbinafine tablets. Your doctor may also check you for liver problems during treatment, and tell you to stop taking terbinafine tablets if you develop liver problems.

What are Terbinafine tablets?

Terbinafine tablets are prescription medicine used to treat fungal infections of the fingernails and toenails (onychomycosis).

Your doctor should do tests to check you for fungal infection of your nails before you start terbinafine tablets.

It is not known if terbinafine tablets are safe and effective in children for the treatment of onychomycosis.

Who should not take terbinafine tablets?

Do not take terbinafine tablets if you:

- have had a severe allergic reaction to terbinafine hydrochloride when taken by mouth.
- have had liver disease for a long time (chronic) or have active liver disease.

What should I tell my doctor before taking terbinafine tablets?

Before taking terbinafine tablets, tell your doctor about all of your medical conditions, including if you:

- have or had liver problems
- have a weakened immune system (immunocompromised)
- have lupus (an autoimmune disease)
- are pregnant or plan to become pregnant. It is not known if terbinafine tablets may harm your unborn baby.

Tell your doctor right away if you become pregnant during treatment with terbinafine tablets.

- are breastfeeding or plan to breastfeed. Terbinafine hydrochloride passes into your breast milk and may harm your baby. Talk to your doctor about the best way to feed your baby if you take terbinafine tablets.

Tell your doctor about all the medicines you take, including prescription and over-the-counter medicines, vitamins, and herbal supplements. Terbinafine tablets may affect the way other medicines work and other medicines may affect how terbinafine tablets work.

How should I take terbinafine tablets?

- Take terbinafine tablets exactly as your doctor tells you to take them.
- Terbinafine hydrochloride comes as a tablet that you take by mouth.
- Terbinafine tablets are usually taken:
- 1 time each day for 6 weeks to treat fungal infections of your fingernail, or
- 1 time each day for 12 weeks to treat fungal infections of your toenail
- Terbinafine tablets can be taken with or without food.
- If you miss a dose of terbinafine tablets, take it as soon as you remember. If it is less than 4 hours before your next dose, skip the missed dose. Just take the next dose at your regular time.

If you take too many terbinafine tablets, call your doctor. You may have the following symptoms:

- nausea
- vomiting
- stomach-area (abdomen) pain
- dizziness
- rash
- frequent urination
- headache

What should I avoid while taking terbinafine tablets?

Avoid sunlight. Terbinafine tablets can make your skin sensitive to the sun and the light from sunlamps and tanning beds. You can get a severe sunburn. Use sunscreen and wear a hat and clothes that cover your skin if you have to be in sunlight. Talk to your doctor if you get sunburn.

What are the possible side effects of terbinafine tablets?

Terbinafine tablets may cause serious side effects, including:

- See "What is the most important information I should know about terbinafine tablets?"
- Change in your sense of taste or loss of taste is common with terbinafine tablets, but can also be severe. This may improve within several weeks after you stop taking terbinafine tablets, but may last for a long time or may become permanent. Tell your doctor if you develop any of the following:
  - change in your sense of taste or loss of taste
  - poor appetite
  - change in your mood or depressive symptoms.
  - weight loss
  - anxiousness

See the list of depressive symptoms below.

- Change in your sense of smell or loss of smell may happen with terbinafine tablets. This may improve after you stop taking terbinafine tablets, but may last for a long time or may become permanent. Tell your doctor if you have a change in your sense of smell or loss of smell.
- Depressive symptoms. Tell your doctor right away if you develop any of these signs or symptoms:
  - feel sad or worthless
  - change in sleep pattern
  - loss of energy or interest in daily activities
  - restlessness
  - mood changes

- Low white blood cell count. Terbinafine tablets may decrease your white blood cell count, especially neutrophils. You may have a higher risk of getting an infection when your white blood cell count is low.
- Serious skin or allergic reactions, which may include problems with some of your body organs . Tell your doctor right away or get emergency medicalhelp if you get any of these symptoms:
  - skin rash
  - hives
  - sores in your mouth, or your skin blisters and peels
  - swelling of your face, eyes, lips, tongue or throat
  - trouble swallowing or breathing
  - fever
  - swollen lymph glands

Also tell your doctor about any new symptoms, such as cough, chest pain, fast heartbeat, or blood in your urine.

- New or worsening lupus. Stop taking terbinafine tablets and tell your doctor if you get any of the following:
  - a skin rash that gets worse (progresses), is scaly, red, shows scarring, or loss of skin color
  - unusual sensitivity to the sun that can cause a rash

- Blood clotting problems . When taking terbinafine tablets, you may develop a blood clotting problem that can sometimes cause death. Tell your doctor, if you get any unexplained bleeding or bruising.

The most common side effects of terbinafine tablets include:

- headache
- diarrhea
- rash
- upset stomach
- abnormal liver function tests
- itching
- nausea
- stomach-area (abdomen) pain
- gas

These are not all of the possible side effects of terbinafine tablets.

Call your doctor for medical advice about side effects. You may report side effects to FDA at 1-800-FDA-1088.

How should I store terbinafine tablets?

- Store terbinafine tablets at 20°C to 25°C (68° to 77°F)
- Keep terbinafine tablets in a tightly closed container and keep out of the light.

Keep terbinafine tablets and all medicines out of the reach of children.

General information about the safe and effective use of terbinafine tablets.

Medicines are sometimes prescribed for purposes other than those listed in Medication Guide. Do not use terbinafine tablets for a condition for which it was not prescribed. Do not give terbinafine tablets to other people, even if they have the same symptoms that you have. They may harm them. You can ask your pharmacist or doctor for information about terbinafine tablets that is written for health professionals.

What are the ingredients in terbinafine tablets?

Active ingredient: Terbinafine hydrochloride

Inactive ingredients: Colloidal silicon dioxide, croscarmellose sodium, hypromellose, magnesium stearate, microcrystalline cellulose.

This Medication Guide has been approved by the U.S. Food and Drug Administration

Dispense with Medication Guide available at: www.amicipharma.com/products

Distributed by:

Amici Pharma, Inc.

Melville, NY 11747

Code: L7225

Revised: 11/2025

PACKAGE LABEL.PRINCIPAL DISPLAY PANEL

NDC 69292-225-30

Rx only

Terbinafine Tablets, USP

250 mg

30 Tablets

Amici Pharma, Inc.

PACKAGE LABEL.PRINCIPAL DISPLAY PANEL

NDC 69292-225-01

Rx only

Terbinafine Tablets, USP

250 mg

100 Tablets

Amici Pharma, Inc.